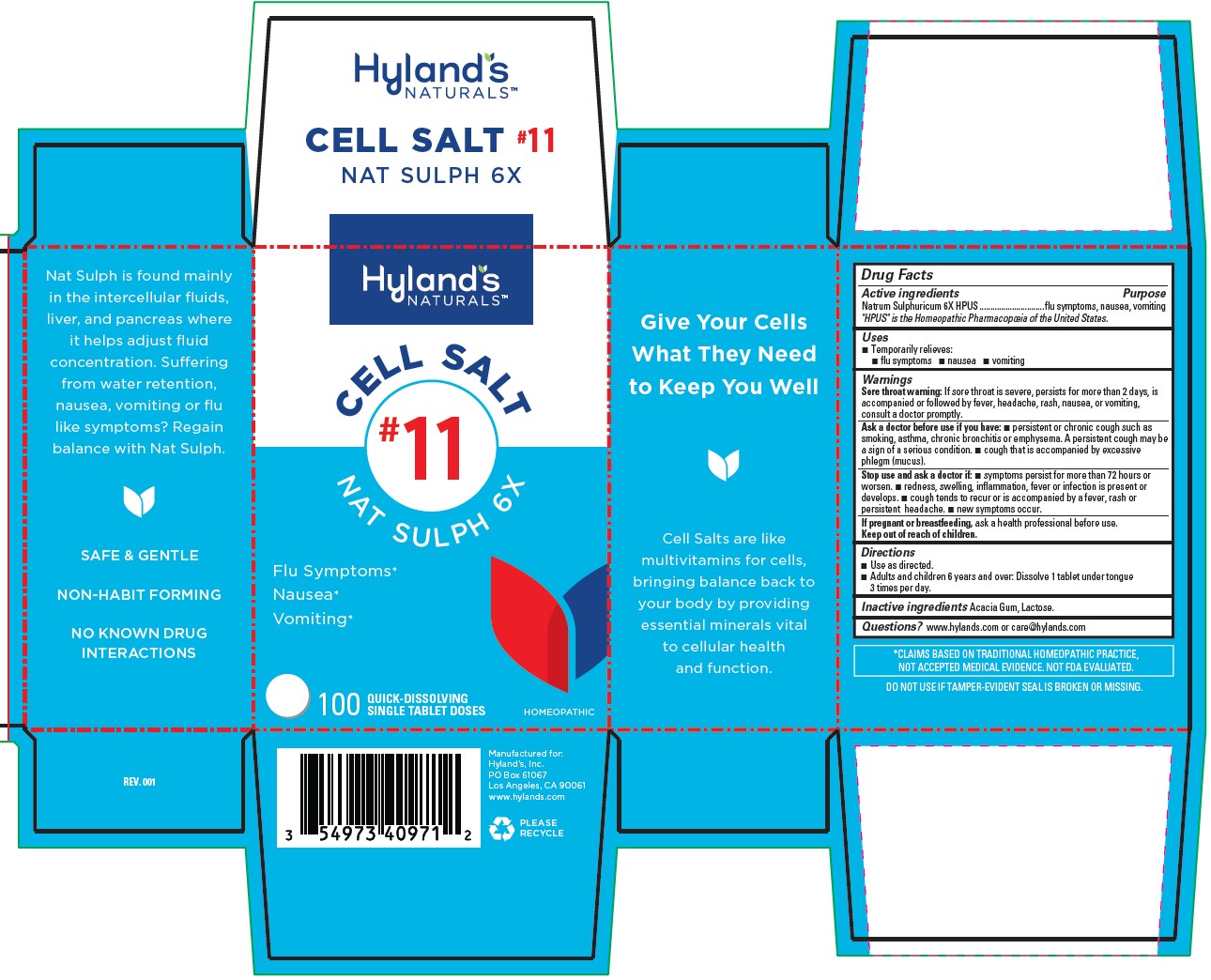 DRUG LABEL: NAT SULPH 6X
NDC: 54973-4097 | Form: TABLET, SOLUBLE
Manufacturer: Hyland's Inc.
Category: homeopathic | Type: HUMAN OTC DRUG LABEL
Date: 20221213

ACTIVE INGREDIENTS: SODIUM SULFATE 6 [hp_X]/1 1
INACTIVE INGREDIENTS: ACACIA; LACTOSE MONOHYDRATE

Cell Salt #11 NAT SULPH 6X

PURPOSE

Flu Symptoms*

Nausea*

Vomiting*

Drug Facts

Active ingredients | Purpose
Natrum Sulphuricum 6X HPUS | flu symptoms, nausea, vomiting

"HPUS" is the Homeopathic Pharmacopoeia of the United States.

Uses

■ Temporarily relieves:
■ flu symptoms ■ nausea ■ vomiting

Warnings

Sore throat warning

If sore throat is severe, persists for more than 2 days, is accompanied or followed by fever, headache, rash, nausea, or vomiting,
consult a doctor promptly.

Ask a doctor before use if you have

■ persistent or chronic cough such as smoking, asthma, chronic bronchitis or emphysema. A persistent cough may be
a sign of a serious condition. ■ cough that is accompanied by excessive phlegm (mucus).

Stop use and ask a doctor if

■ symptoms persist for more than 72 hours or worsen. ■ redness, swelling, inflammation, fever or infection is present or develops.

■ cough tends to recur or is accompanied by a fever, rash or persistent headache. ■ new symptoms occur.

If pregnant or breastfeeding

Ask a health professional before use.

Directions

■ Use as directed.
■ Adults and children 6 years and over: Dissolve 1 tablet under tongue 3 times per day.

Inactive ingredients

Acacia Gum, Lactose.

Questions?

www.hylands.com or care@hylands.com

PRINCIPAL DISPLAY PANEL

Hyland's

NATURALS™

CELL SALT

#11

NAT SULPH 6X

Flu Symptoms*

Nausea*

Vomiting*

100

QUICK-DISSOLVING

SINGLE TABLET DOSE

HOMEOPATHIC